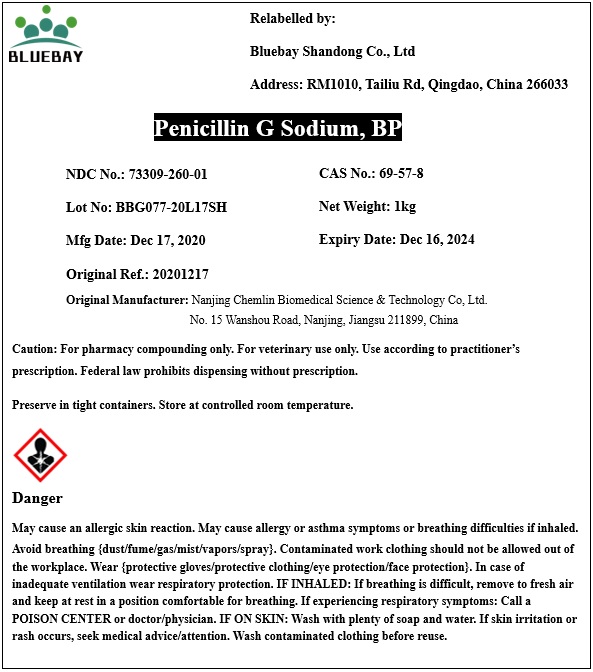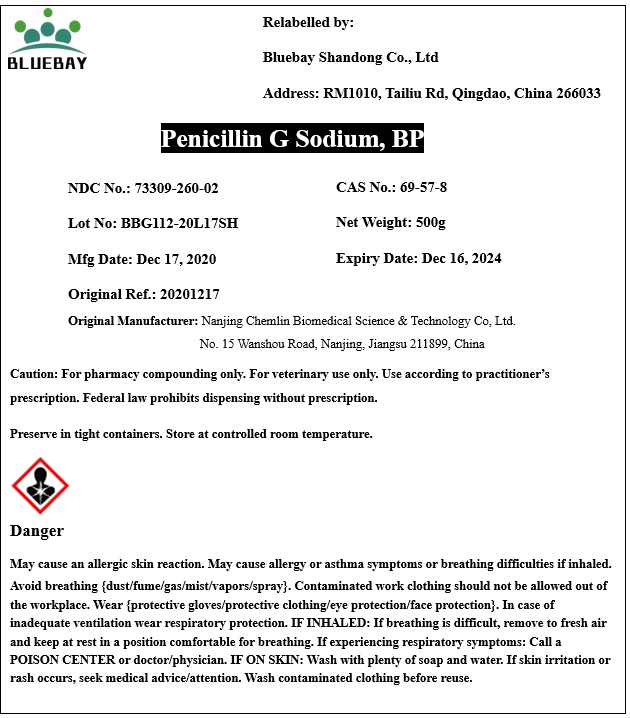 DRUG LABEL: Penicillin G Sodium
NDC: 73309-260 | Form: POWDER
Manufacturer: BLUEBAY SHANDONG CO.,LTD
Category: other | Type: BULK INGREDIENT
Date: 20210324

ACTIVE INGREDIENTS: PENICILLIN G SODIUM 1 kg/1 kg

Penicillin G Sodium